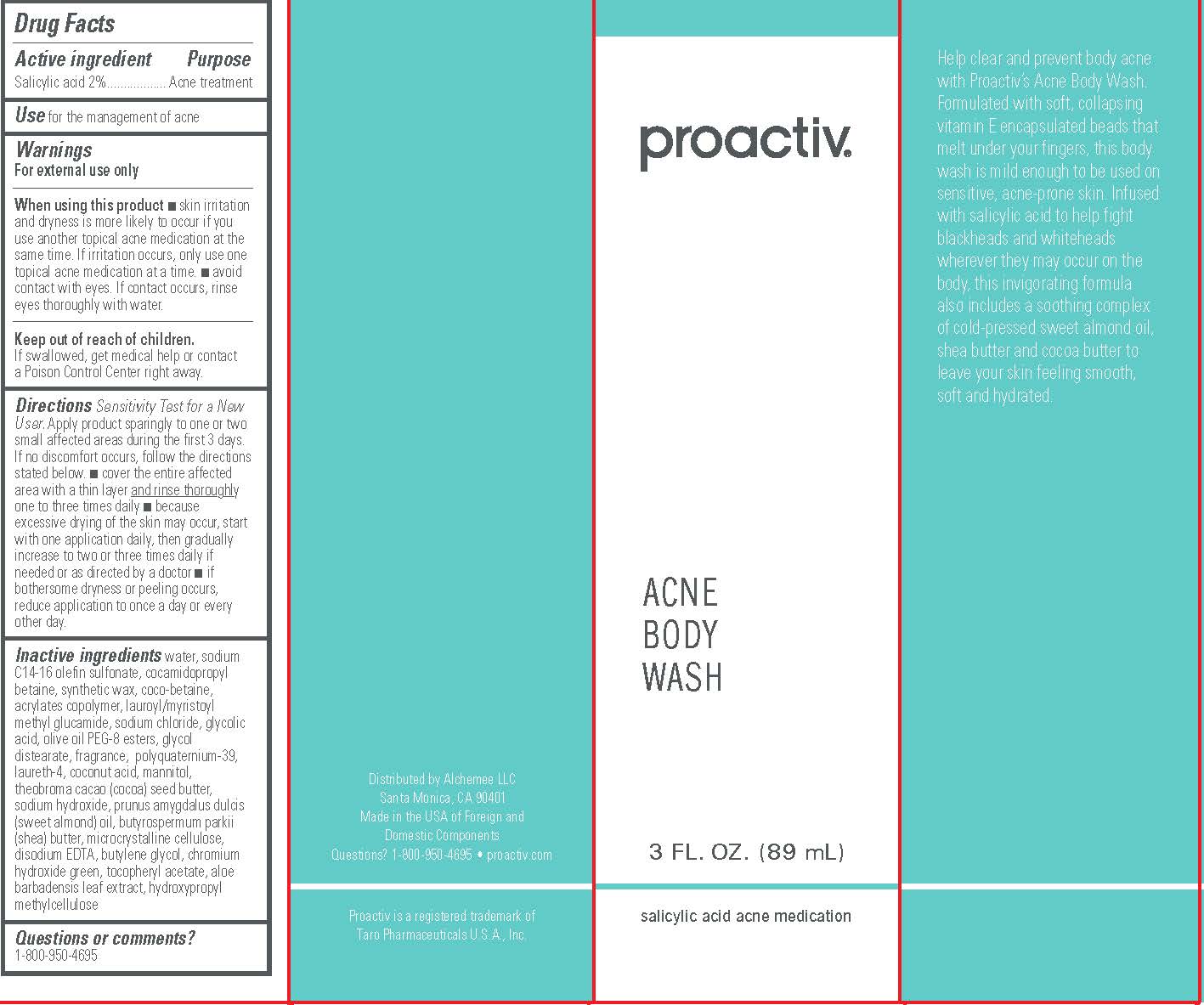 DRUG LABEL: Proactiv Acne Body Wash
NDC: 11410-074 | Form: LIQUID
Manufacturer: Alchemee, LLC
Category: otc | Type: HUMAN OTC DRUG LABEL
Date: 20260107

ACTIVE INGREDIENTS: SALICYLIC ACID 2 g/100 mL
INACTIVE INGREDIENTS: WATER; SODIUM C14-16 OLEFIN SULFONATE; OLIVE OIL GLYCERETH-8 ESTERS; GLYCOL DISTEARATE; LAURETH-4; POLYQUATERNIUM-39 (22.5/51/26.5 ACRYLIC ACID/ACRYLAMIDE/DADMAC; 1600000 MW); COCONUT ACID; MANNITOL; COCOA BUTTER; SODIUM HYDROXIDE; ALMOND OIL; SHEA BUTTER; MICROCRYSTALLINE CELLULOSE; EDETATE DISODIUM; BUTYLENE GLYCOL; CHROMIUM HYDROXIDE GREEN; .ALPHA.-TOCOPHEROL ACETATE; ALOE VERA LEAF; HYPROMELLOSE, UNSPECIFIED; COCAMIDOPROPYL BETAINE; SYNTHETIC WAX (1200 MW); COCO-BETAINE; LAUROYL/MYRISTOYL METHYL GLUCAMIDE; SODIUM CHLORIDE; GLYCOLIC ACID

Proactiv Acne Body Wash

Active Ingredient

Salicylic Acid 2%

Purpose

Acne Treatment

Use

For the management of acne

Warnings

For external use only
When using this product ▪ skin irritation and dryness is more likely to occur if you use another topical acne medication at the same time. If irritation occurs, only use one topical acne medication at a time. ▪ avoid contact with eyes. If contact occurs, rinse eyes thoroughly with water.

Directions

- Sensitivity Test for a New User. Apply product sparingly to one or two small affected areas during the first 3 days. If no discomfort occurs, follow the directions stated below.
- cover the entire affected area with a thin layer and rinse thoroughlyone to three times daily
- because excessive drying of the skin may occur, start with one application daily, then gradually increase to two or three times daily if needed or as directed by a doctor
- if bothersome dryness or peeling occurs, reduce application to once a day or every other day.

Inactive Ingredients

water, sodium C14-16 olefin sulfonate, cocamidopropyl betaine, synthetic wax, coco-betaine, acrylates copolymer, lauroyl/myristoyl methyl glucamide, sodium chloride, glycolic acid, olive oil PEG-8 esters, glycol distearate, fragrance, polyquaternium-39, laureth-4, coconut acid, mannitol, theobroma cacao (cocoa) seed butter, sodium hydroxide, prunus amygdalus dulcis (sweet almond) oil, butyrospermum parkii (shea) butter, microcrystalline cellulose, disodium EDTA, butylene glycol, chromium hydroxide green, tocopheryl acetate, aloe barbadensis leaf extract, hydroxypropyl methylcellulose

Questions or comments?
1-800-950-4695

Distributed by Alchemee LLC
Santa Monica, CA 90401
Made in the USA of Foreign and
Domestic Components
Questions? 1-800-950-4695 • proactiv.com
Proactiv is a registered trademark of
Taro Pharmaceuticals U.S.A., Inc.

PRINCIPAL DISPLAY PANEL - 89 mL

proactiv®
ACNE
BODY
WASH
3 FL. OZ. (89 mL)
salicylic acid acne medication